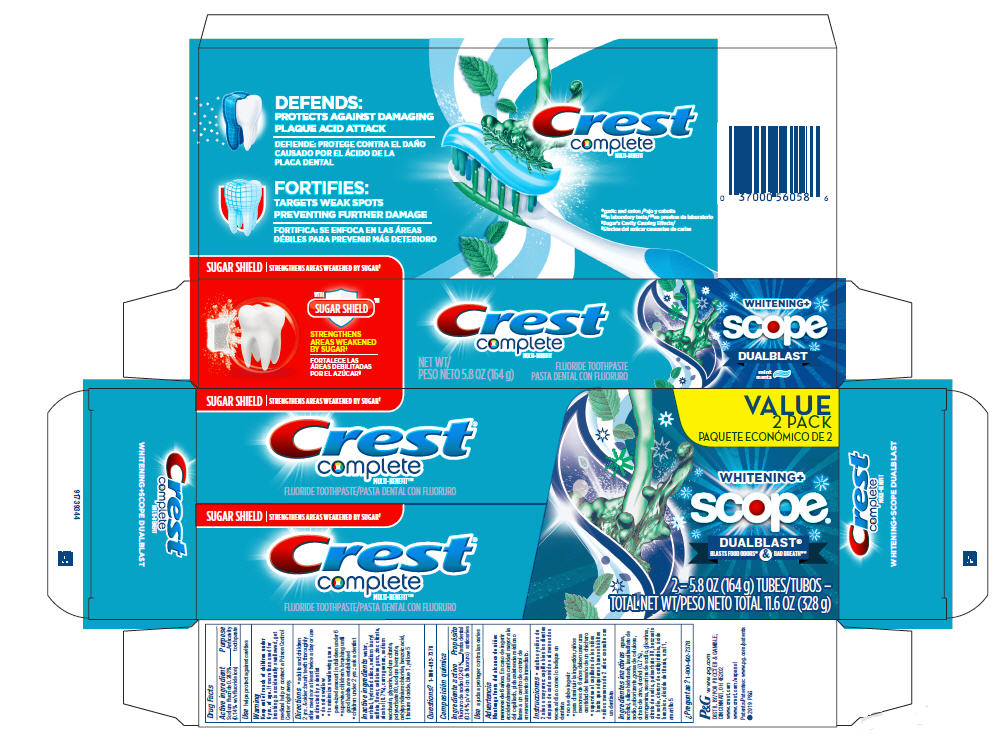 DRUG LABEL: Crest Complete Multi-Benefit
NDC: 37000-948 | Form: PASTE, DENTIFRICE
Manufacturer: The Procter & Gamble Manufacturing Company
Category: otc | Type: HUMAN OTC DRUG LABEL
Date: 20250806

ACTIVE INGREDIENTS: SODIUM FLUORIDE 1.4 mg/1 g
INACTIVE INGREDIENTS: ALCOHOL; CARBOXYMETHYLCELLULOSE SODIUM; CARRAGEENAN; GLYCERIN; SODIUM CITRATE; POLYSORBATE 80; SODIUM BENZOATE; CETYLPYRIDINIUM CHLORIDE; SORBITOL; BENZOIC ACID; TITANIUM DIOXIDE; FD&C BLUE NO. 1; FD&C YELLOW NO. 5; SACCHARIN SODIUM; WATER; HYDRATED SILICA; SODIUM LAURYL SULFATE; ZINC CITRATE

Crest complete Multi-Benefit Whitening+ Scope Outlast

Drug Facts

Active ingredient

Sodium fluoride 0.243%

(0.14% w/v fluoride ion)

Purpose

Anticavity toothpaste

Use

helps protect against cavities

Warnings

Keep out of reach of children under 6 yrs. of age. If more than used for brushing is accidentally swallowed, get medical help or contact a Poison Control Center right away.

Directions

- adults and children 2 yrs. & older: brush teeth thoroughly after meals or at least twice a day or use as directed by a dentist
- do not swallow
- to minimize swallowing use a pea-sized amount in children under 6
- supervise children's brushing until good habits are established
- children under 2 yrs.: ask a dentist

Inactive ingredients

water, sorbitol, hydrated silica, sodium lauryl sulfate, flavor, cellulose gum, zinc citrate, alcohol (0.7%), carrageenan, sodium saccharin, glycerin, sodium citrate, polysorbate 80, sodium benzoate, cetylpyridinium chloride, benzoic acid, titanium dioxide, blue 1, yellow 5

Questions?

1-800-492-7378

DISTR. BY PROCTER & GAMBLE,
CINCINNATI, OH 45202

PRINCIPAL DISPLAY PANEL - 164 g Tube Carton

Crest ®
complete

MULTI-BENEFIT™

FLUORIDE TOOTHPASTE

WHITENING+

scope®

DUALBLAST®
BLASTS FOOD ODORS* &BAD BREATH**
2 - 5.8 OZ (164g) TUBES
TOTAL NET WT 11.6 OZ (328 g)